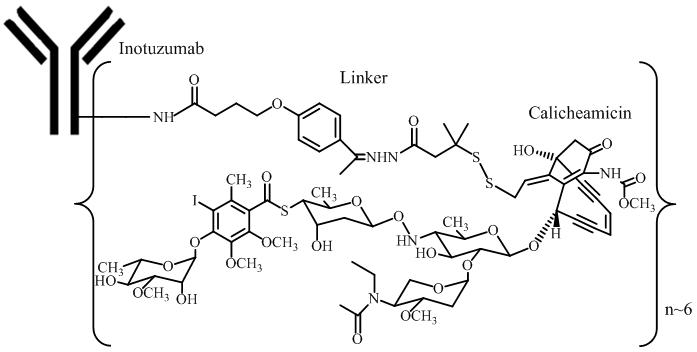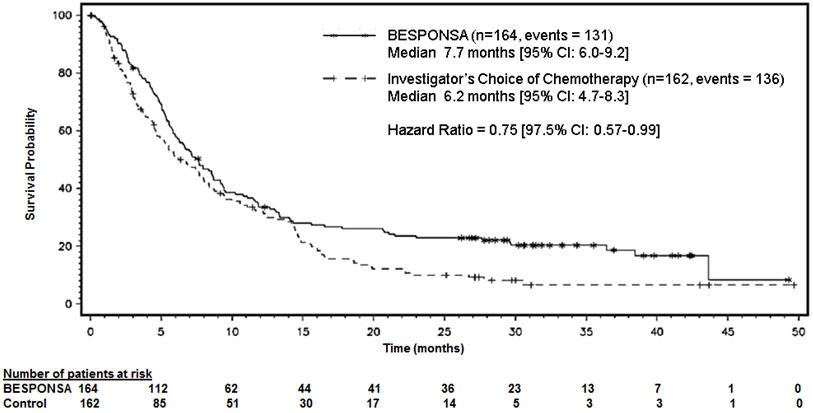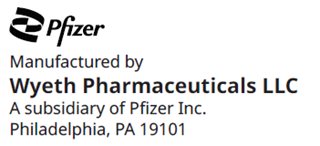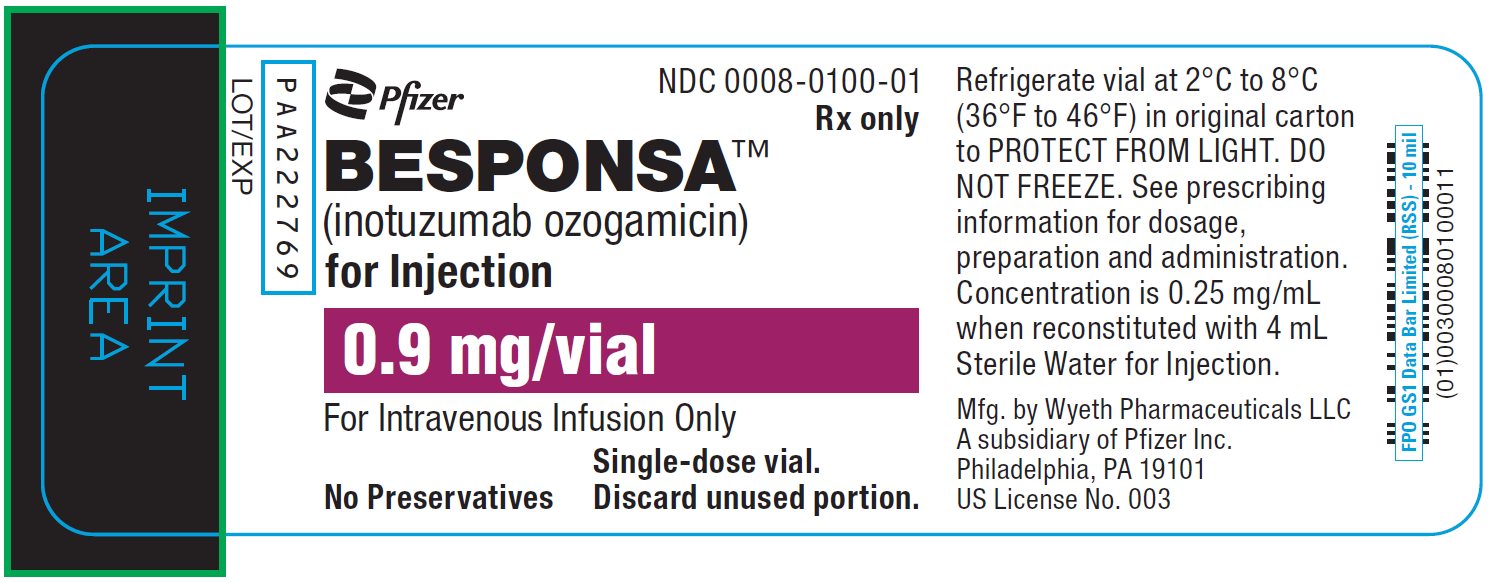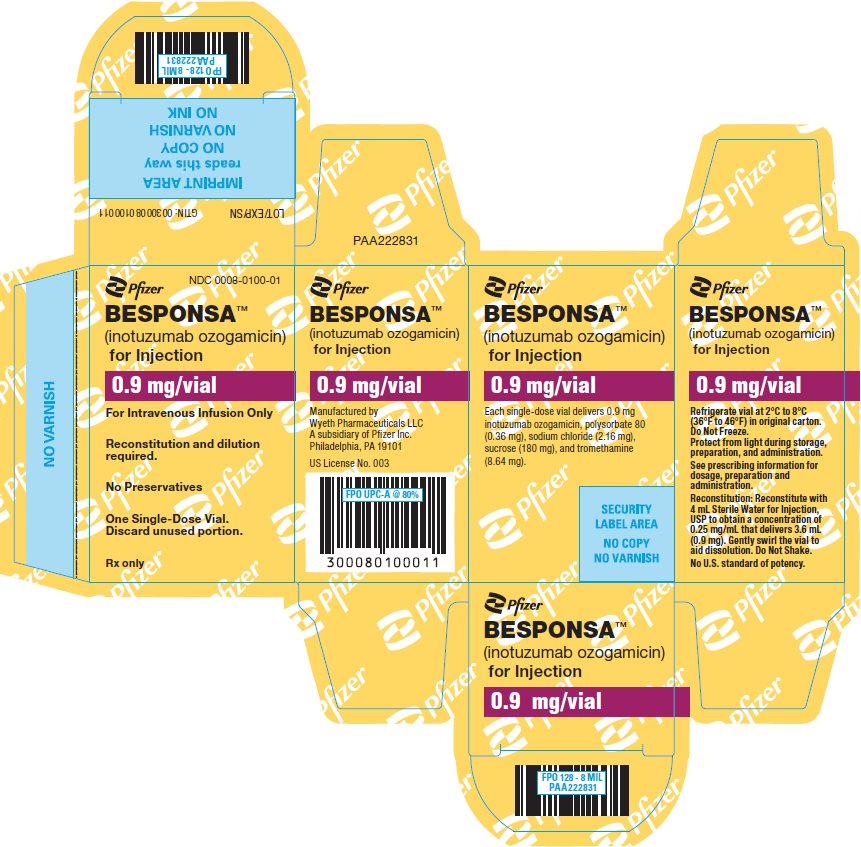 DRUG LABEL: Besponsa
NDC: 0008-0100 | Form: INJECTION, POWDER, LYOPHILIZED, FOR SOLUTION
Manufacturer: Wyeth Pharmaceuticals LLC, a subsidiary of Pfizer Inc.
Category: prescription | Type: HUMAN PRESCRIPTION DRUG LABEL
Date: 20260206

ACTIVE INGREDIENTS: INOTUZUMAB OZOGAMICIN 0.25 mg/1 mL
INACTIVE INGREDIENTS: TROMETHAMINE; SUCROSE; POLYSORBATE 80; SODIUM CHLORIDE; WATER

HIGHLIGHTS OF PRESCRIBING INFORMATION

These highlights do not include all the information needed to use BESPONSA™ safely and effectively. See full prescribing information for BESPONSA.
BESPONSA (inotuzumab ozogamicin) for injection, for intravenous use
Initial U.S. Approval: 2017

RECENT MAJOR CHANGES

Indications and Usage (1) | 3/2024
Dosage and Administration, Instructions for Reconstitution, Dilution and Administration (2.4) | 3/2024
Warnings and Precautions, Hepatotoxicity, Including Hepatic Veno-occlusive Disease (VOD) (also known as Sinusoidal Obstruction Syndrome) (5.1) | 3/2024
Warnings and Precautions, Increased Risk of Post-Transplant Non-Relapse Mortality (5.2) | 3/2024
Warnings and Precautions, Myelosuppression (5.3) | 3/2024
Warnings and Precautions, Infusion Related Reactions (5.4) | 3/2024
Warnings and Precautions, QT Interval Prolongation (5.5) | 3/2024

WARNING: HEPATOTOXICITY, INCLUDING HEPATIC VENO-OCCLUSIVE DISEASE (VOD) (ALSO KNOWN AS SINUSOIDAL OBSTRUCTION SYNDROME) and INCREASED RISK OF POST-HEMATOPOIETIC STEM CELL TRANSPLANT (HSCT) NON-RELAPSE MORTALITY

See full prescribing information for complete boxed warning.

- Hepatotoxicity, including fatal and life-threatening VOD occurred in patients who received BESPONSA. (5.1)
- A higher post-HSCT non-relapse mortality rate occurred in patients receiving BESPONSA (5.2)

1. INDICATIONS AND USAGE

BESPONSA is a CD22-directed antibody and cytotoxic drug conjugate indicated for the treatment of relapsed or refractory CD22-positive B-cell precursor acute lymphoblastic leukemia (ALL) in adult and pediatric patients 1 year and older. (1)

2. DOSAGE AND ADMINISTRATION

- Administer by intravenous infusion only. (2.1)
- Pre-medicate with a corticosteroid, antipyretic, and antihistamine prior to all infusions. (2.2)
- Dosing regimens for Cycle 1 and subsequent cycles, depending on the response to treatment, are shown below. See full prescribing information for dosing details. (2)

 | Day 1 | Day 8 | Day 15
Dosing regimen for Cycle 1
All patients:
Dose | 0.8 mg/m^2 | 0.5 mg/m^2 | 0.5 mg/m^2
Cycle length | 21 days [For patients who achieve a CR or a CRi, and/or to allow for recovery from toxicity, the cycle length may be extended up to 28 days (i.e., 7-day treatment-free interval starting on Day 21).]
Dosing regimen for subsequent cycles depending on response to treatment
Patients who have achieved a CR or CRi:
Dose | 0.5 mg/m^2 | 0.5 mg/m^2 | 0.5 mg/m^2
Cycle length | 28 days
Patients who have not achieved a CR or CRi:
Dose | 0.8 mg/m^2 | 0.5 mg/m^2 | 0.5 mg/m^2
Cycle length | 28 days

- See full prescribing information for instructions on reconstitution of lyophilized powder, and preparation and administration of reconstituted drug. (2.4)

3. DOSAGE FORMS AND STRENGTHS

For injection: 0.9 mg lyophilized powder in a single-dose vial for reconstitution and further dilution. (3)

4. CONTRAINDICATIONS

None (4)

5. WARNINGS AND PRECAUTIONS

- Myelosuppression: Monitor complete blood counts; for signs and symptoms of infection; bleeding/hemorrhage; or other effects of myelosuppression during treatment; manage appropriately. (5.3)
- Infusion related reactions: Monitor for infusion related reactions during and for at least 1 hour after infusion ends. (5.4)
- QT interval prolongation: Obtain electrocardiograms (ECGs) and electrolytes at baseline and monitor during treatment. Monitor more frequently when using concomitant mediations known to prolong QT interval. (5.5)
- Embryo-fetal toxicity: Can cause fetal harm. Advise females of reproductive potential of the potential risk to a fetus and to use effective contraception. (5.6, 8.1, 8.3)

6. ADVERSE REACTIONS

The most common (≥ 20%) adverse reactions, including laboratory abnormalities, in adult and pediatric patients are thrombocytopenia, pyrexia, neutropenia, infection, anemia, vomiting, leukopenia, hemorrhage, fatigue, nausea, febrile neutropenia, headache, transaminases increased, abdominal pain, and gamma-glutamyltransferase increased, and hyperbilirubinemia. (6.1)

To report SUSPECTED ADVERSE REACTIONS, contact Pfizer Inc at 1-800-438-1985 or FDA at 1-800-FDA-1088 or www.fda.gov/medwatch.

8. USE IN SPECIFIC POPULATIONS

Lactation: Advise not to breastfeed. (8.2)

FULL PRESCRIBING INFORMATION

WARNING: HEPATOTOXICITY, INCLUDING HEPATIC VENO-OCCLUSIVE DISEASE (VOD) (ALSO KNOWN AS SINUSOIDAL OBSTRUCTION SYNDROME) and INCREASED RISK OF POST-HEMATOPOIETIC STEM CELL TRANSPLANT (HSCT) NON-RELAPSE MORTALITY

HEPATOTOXICITY, INCLUDING VOD

- Hepatotoxicity, including fatal and life-threatening VOD occurred in patients with relapsed or refractory acute lymphoblastic leukemia (ALL) who received BESPONSA. The risk of VOD was greater in patients who underwent HSCT after BESPONSA treatment; use of HSCT conditioning regimens containing 2 alkylating agents and last total bilirubin level ≥ upper limit of normal (ULN) before HSCT were significantly associated with an increased risk of VOD.
- Other risk factors for VOD in patients treated with BESPONSA included ongoing or prior liver disease, prior HSCT, increased age, later salvage lines, and a greater number of BESPONSA treatment cycles.
- Elevation of liver tests may require dosing interruption, dose reduction, or permanent discontinuation of BESPONSA. Permanently discontinue treatment if VOD occurs. If severe VOD occurs, treat according to standard medical practice [see Dosage and Administration (2.3) and Warnings and Precautions (5.1)].

INCREASED RISK OF POST-HSCT NON-RELAPSE MORTALITY

- There was higher post-HSCT non-relapse mortality rate in patients receiving BESPONSA, resulting in a higher Day 100 post-HSCT mortality rate [see Warnings and Precautions (5.2)].

1. INDICATIONS AND USAGE

BESPONSA is indicated for the treatment of relapsed or refractory CD22-positive B-cell precursor acute lymphoblastic leukemia (ALL) in adult and pediatric patients 1 year and older.

2. DOSAGE AND ADMINISTRATION

2.1 Recommended Dosage

- Pre-medicate before each dose [see Dosage and Administration (2.2)].
- Administer by intravenous infusion only.
- For the first cycle, the recommended total dose of BESPONSA for all patients is 1.8 mg/m^2 per cycle, administered as 3 divided doses on Day 1 (0.8 mg/m^2), Day 8 (0.5 mg/m^2), and Day 15 (0.5 mg/m^2). Cycle 1 is 3 weeks in duration, but may be extended to 4 weeks if the patient achieves a complete remission (CR) or complete remission with incomplete hematologic recovery (CRi), and/or to allow recovery from toxicity.
- For subsequent cycles:
  - In patients who achieve a CR or CRi, the recommended total dose of BESPONSA is 1.5 mg/m^2 per cycle, administered as 3 divided doses on Day 1 (0.5 mg/m^2), Day 8 (0.5 mg/m^2), and Day 15 (0.5 mg/m^2). Subsequent cycles are 4 weeks in duration.
    OR
  - In patients who do not achieve a CR or CRi, the recommended total dose of BESPONSA is 1.8 mg/m^2 per cycle given as 3 divided doses on Day 1 (0.8 mg/m^2), Day 8 (0.5 mg/m^2), and Day 15 (0.5 mg/m^2). Subsequent cycles are 4 weeks in duration. Patients who do not achieve a CR or CRi within 3 cycles should discontinue treatment.
- For patients proceeding to hematopoietic stem cell transplant (HSCT), the recommended duration of treatment with BESPONSA is 2 cycles. A third cycle may be considered for those patients who do not achieve CR or CRi and minimal residual disease (MRD) negativity after 2 cycles [see Warnings and Precautions (5.1)].
- For patients not proceeding to HSCT, additional cycles of treatment, up to a maximum of 6 cycles, may be administered.

Table 1 shows the recommended dosing regimens.

Table 1. Dosing Regimen for Cycle 1 and Subsequent Cycles Depending on Response to Treatment
 | Day 1 | Day 8 [+/- 2 days (maintain minimum of 6 days between doses).] | Day 15
Dosing regimen for Cycle 1
All patients:
Dose [Dose is based on the patient's body surface area (m^2).] | 0.8 mg/m^2 | 0.5 mg/m^2 | 0.5 mg/m^2
Cycle length | 21 days [For patients who achieve a CR or a CRi, and/or to allow for recovery from toxicity, the cycle length may be extended up to 28 days (i.e., 7-day treatment-free interval starting on Day 21).]
Dosing regimen for subsequent cycles depending on response to treatment
Patients who have achieved a CR [CR is defined as < 5% blasts in the bone marrow and the absence of peripheral blood leukemic blasts, full recovery of peripheral blood counts (platelets ≥ 100 × 10^9/L and absolute neutrophil counts [ANC] ≥ 1 × 10^9/L) and resolution of any extramedullary disease.] or CRi [CRi is defined as < 5% blasts in the bone marrow and the absence of peripheral blood leukemic blasts, incomplete recovery of peripheral blood counts (platelets < 100 × 10^9/L and/or ANC < 1 × 10^9/L) and resolution of any extramedullary disease.] :
Dose | 0.5 mg/m^2 | 0.5 mg/m^2 | 0.5 mg/m^2
Cycle length | 28 days [7-day treatment-free interval starting on Day 21.]
Patients who have not achieved a CR or CRi:
Dose | 0.8 mg/m^2 | 0.5 mg/m^2 | 0.5 mg/m^2
Cycle length | 28 days
Abbreviations: CR=complete remission; CRi=complete remission with incomplete hematologic recovery.

2.2 Recommended Pre-medications and Cytoreduction

- Premedication with a corticosteroid, antipyretic, and antihistamine is recommended prior to dosing. Patients should be observed during and for at least 1 hour after the end of infusion for symptoms of infusion related reactions [see Warnings and Precautions (5.4)].
- For patients with circulating lymphoblasts, cytoreduction with a combination of hydroxyurea, steroids, and/or vincristine to a peripheral blast count of less than or equal to 10,000/mm^3 is recommended prior to the first dose.

2.3 Dosage Modifications for Adverse Reactions

Modify the dose of BESPONSA for toxicities (see Tables 2–4). BESPONSA doses within a treatment cycle (i.e., Days 8 and/or 15) do not need to be interrupted due to neutropenia or thrombocytopenia, but dosing interruptions within a cycle are recommended for non-hematologic toxicities. If the dose is reduced due to BESPONSA-related toxicity, the dose must not be re-escalated.

Table 2. BESPONSA Dosage Modifications for Hematologic Toxicities [see Warnings and Precautions (5.3)]

Criteria | BESPONSA Dosage Modification(s)
If prior to BESPONSA treatment ANC was greater than or equal to 1 × 10^9/L | If ANC decreases, then interrupt the next cycle of treatment until recovery of ANC to greater than or equal to 1 × 10^9/L. Discontinue BESPONSA if low ANC persists for greater than 28 days and is suspected to be related to BESPONSA.
If prior to BESPONSA treatment platelet count was greater than or equal to 50 × 10^9/L [Platelet count used for dosing should be independent of blood transfusion.] | If platelet count decreases, then interrupt the next cycle of treatment until platelet count recovers to greater than or equal to 50 × 10^9/L. Discontinue BESPONSA if low platelet count persists for greater than 28 days and is suspected to be related to BESPONSA.
If prior to BESPONSA treatment ANC was less than 1 × 10^9/L and/or platelet count was less than 50 × 10^9/L | If ANC or platelet count decreases, then interrupt the next cycle of treatment until at least one of the following occurs:; - ANC and platelet counts recover to at least baseline levels for the prior cycle, or - ANC recovers to greater than or equal to 1 × 10^9/L and platelet count recovers to greater than or equal to 50 × 10^9/L, or - Stable or improved disease (based on most recent bone marrow assessment) and the ANC and platelet count decrease is considered to be due to the underlying disease (not considered to be BESPONSA-related toxicity).
Abbreviation: ANC=absolute neutrophil count.

Table 3. BESPONSA Dosage Modifications for Non-hematologic Toxicities
Non-hematologic Toxicity | Dosage Modification(s)
VOD or other severe liver toxicity | Permanently discontinue treatment [see Warnings and Precautions (5.1)].
Total bilirubin greater than 1.5 × ULN and AST/ALT greater than 2.5 × ULN | Interrupt dosing until recovery of total bilirubin to less than or equal to 1.5 × ULN and AST/ALT to less than or equal to 2.5 × ULN prior to each dose unless due to Gilbert's syndrome or hemolysis. Permanently discontinue treatment if total bilirubin does not recover to less than or equal to 1.5 × ULN or AST/ALT does not recover to less than or equal to 2.5 × ULN [see Warnings and Precautions (5.1)].
Infusion related reaction | Interrupt the infusion and institute appropriate medical management. Depending on the severity of the infusion related reaction, consider discontinuation of the infusion or administration of steroids and antihistamines. For severe or life-threatening infusion reactions, permanently discontinue treatment [see Warnings and Precautions (5.4)].
Non-hematologic toxicity greater than or equal to Grade 2 [Severity grade according to National Cancer Institute Common Terminology Criteria for Adverse Events (NCI CTCAE) version 3.0.] | Interrupt treatment until recovery to Grade 1 or pre-treatment grade levels prior to each dose.
Abbreviations: ALT=alanine aminotransferase; AST=aspartate aminotransferase; ULN=upper limit of normal; VOD=veno‑occlusive disease.

Table 4. BESPONSA Dosage Modifications Depending on Duration of Dosing Interruption Due to Non-Hematologic Toxicity Toxicities
Duration of Dose Interruption Due to Toxicity | Dosage Modification(s)
Less than 7 days (within a cycle) | Interrupt the next dose (maintain a minimum of 6 days between doses).
Greater than or equal to 7 days | Omit the next dose within the cycle.
Greater than or equal to 14 days | Once adequate recovery is achieved, decrease the total dose by 25% for the subsequent cycle. If further dose modification is required, then reduce the number of doses to 2 per cycle for subsequent cycles. If a 25% decrease in the total dose followed by a decrease to 2 doses per cycle is not tolerated, then permanently discontinue treatment.
Greater than 28 days | Consider permanent discontinuation of treatment.

2.4 Instructions for Reconstitution, Dilution, and Administration

Protect the reconstituted and diluted BESPONSA solutions from light. Do not freeze the reconstituted or diluted solution.

The maximum time from reconstitution through the end of administration should be less than or equal to 8 hours, with less than or equal to 4 hours between reconstitution and dilution.

Reconstitution:

- BESPONSA is a hazardous drug. Follow applicable special handling and disposal procedures.^1
- Calculate the dose (mg) and number of vial(s) of BESPONSA required.
- Reconstitute each vial with 4 mL of Sterile Water for Injection, USP, to obtain a concentration of 0.25 mg/mL of BESPONSA that delivers 3.6 mL (0.9 mg).
- Gently swirl the vial to aid dissolution. DO NOT SHAKE.
- Inspect the reconstituted solution for particulates and discoloration. The reconstituted solution should be clear to opalescent, colorless to slightly yellow, and essentially free of visible foreign matter.
- See Table 6 for storage times and conditions for the reconstituted solution.

Dilution:

- Withdraw the required volume of the reconstituted solution from the vial(s) needed to obtain the appropriate dose according to the patient’s body surface area. Discard any unused reconstituted BESPONSA solution left in the vial.
- Dilute the reconstituted BESPONSA solution in 0.9% Sodium Chloride Injection, USP, in the appropriate infusion container per Table 5:

Table 5. Infusion Container Information
Infusion Bag Administration | Syringe Administration
- For calculated doses greater than or equal to 0.5 mg - Ensure a final prepared concentration of 0.01 mg/mL to 0.1 mg/mL in a total volume of 50 mL | - For calculated doses less than 0.5 mg - Ensure a final prepared concentration of 0.025 mg/mL to 0.1 mg/mL in a total volume between 2 mL to 50 mL

- Gently invert the infusion container to mix the diluted solution. DO NOT SHAKE.
- PROTECT FROM LIGHT.
- See Table 6 for storage times and conditions for the diluted solution.

Administration:

- See Table 6 for storage times and conditions for prior to and during administration of the diluted solution.
- For syringe infusions, a syringe pump and micro-bore IV tubing must be used.
- Filtration of the diluted solution is not required. However, if the diluted solution is filtered, polyethersulfone (PES)-, polyvinylidene fluoride (PVDF),- or hydrophilic polysulfone (HPS) -based filters are recommended. Do not use filters made of nylon or mixed cellulose ester (MCE).
- Infuse the diluted solution as an intravenous infusion over one hour. Flush the intravenous infusion line with 0.9% Sodium Chloride Injection, USP, to ensure the complete dose is administered.

Do not mix BESPONSA or administer as an infusion with other medicinal products.

Table 6 shows the storage times and conditions for reconstitution, dilution, and administration of BESPONSA.

Table 6. Storage Times and Conditions for Reconstituted and Diluted BESPONSA Solution
 | Storage Time and Conditions [Maximum time from reconstitution through end of administration less than or equal to 8 hours with less than or equal to 4 hours between reconstitution and dilution.]
Reconstituted Solution | - BESPONSA contains no bacteriostatic preservatives. Use reconstituted solution immediately or store refrigerated at (2°C-8°C; 36°F-46°F) for up to 4 hours. - PROTECT FROM LIGHT. DO NOT FREEZE.
Diluted Solution | - Use diluted solution immediately or store at room temperature (20°C-25°C; 68°F-77°F) or refrigerated (2°C-8°C; 36°F-46°F) for up to 6 hours. - If the diluted solution is refrigerated (2°C-8°C; 36°F-46°F), allow it to equilibrate at room temperature (20°C-25°C; 68°F-77°F) for approximately 1 hour prior to administration. - Administer diluted solution within 8 hours of reconstitution including the 1 hour equilibration and 1 hour infusion. - PROTECT FROM LIGHT. DO NOT FREEZE.

3. DOSAGE FORMS AND STRENGTHS

For injection: 0.9 mg as a white to off-white lyophilized powder in a single-dose vial for reconstitution and further dilution.

4. CONTRAINDICATIONS

None.

5. WARNINGS AND PRECAUTIONS

5.1 Hepatotoxicity, Including Hepatic Veno-occlusive Disease (VOD) (also known as Sinusoidal Obstruction Syndrome)

BESPONSA can cause hepatotoxicity, including VOD. In adult patients in the INO-VATE ALL trial, hepatotoxicity, including severe, life-threatening, and sometimes fatal hepatic VOD occurred in 23/164 patients (14%) in the BESPONSA arm during or following treatment or following a HSCT after completion of treatment. VOD occurred up to 56 days after the final dose during treatment or during follow-up without an intervening HSCT. The median time from subsequent HSCT to onset of VOD was 15 days (range: 3-57 days).

In the BESPONSA arm, among the 79 patients who proceeded to a subsequent HSCT, VOD occurred in 18/79 patients (23%), and among all 164 patients treated, VOD occurred in 5/164 patients (3%) during study therapy or in follow-up without an intervening HSCT.

The risk of VOD was greater in patients who underwent HSCT after BESPONSA treatment; use of HSCT conditioning regimens containing 2 alkylating agents (e.g., busulfan in combination with other alkylating agents) and last total bilirubin level greater than or equal to the ULN before HSCT are significantly associated with an increased risk of VOD. Other risk factors for VOD in patients treated with BESPONSA included ongoing or prior liver disease, prior HSCT, increased age, later salvage lines, and a greater number of BESPONSA treatment cycles. Patients who have experienced prior VOD or have serious ongoing hepatic liver disease (e.g., cirrhosis, nodular regenerative hyperplasia, active hepatitis) are at an increased risk for worsening of liver disease, including developing VOD, following treatment with BESPONSA.

In Study WI203581 (ITCC-059) VOD occurred in 8/53 (15%) of pediatric patients treated with single agent BESPONSA. Among the 26 pediatric patients who underwent HSCT, VOD occurred in 5 (19%) patients [see Adverse Reactions (6.1)].

Monitor closely for signs and symptoms of VOD including elevations in total bilirubin, hepatomegaly (which may be painful), rapid weight gain, and ascites. Due to the risk of VOD, for patients proceeding to HSCT, the recommended duration of treatment with BESPONSA is 2 cycles; a third cycle may be considered for those patients who do not achieve a CR or CRi and MRD negativity after 2 cycles [see Dosage and Administration (2.1)]. For patients who proceed to HSCT, monitor liver tests at least weekly during the first month post-HSCT, then less frequently thereafter, according to standard medical practice.

In adult patients in the INO-VATE ALL trial, increases in liver test abnormalities occurred. Grade 3 or 4 AST, ALT, and total bilirubin abnormal liver tests occurred in 7/160 (4%), 7/161 (4%), and 8/161 patients (5%), respectively.

In pediatric patients in Study WI203581 (ITCC-059), liver test abnormalities occurred, with Grade 3 or 4 increases in AST, ALT, and blood bilirubin in 11/53 (21%), 11/53 (21%), and 5/53 (9%) of patients, respectively [see Adverse Reactions (6.1)].

In all patients, monitor liver tests, including ALT, AST, total bilirubin, and alkaline phosphatase, prior to and following each dose of BESPONSA. Based on elevations of liver tests withhold, reduce dose, or permanently discontinue BESPONSA [see Dosage and Administration (2.3)].

5.2 Increased Risk of Post-Transplant Non-Relapse Mortality

In adult patients in the INO-VATE ALL trial, a higher post-HSCT non-relapse mortality rate was observed in patients receiving BESPONSA compared to the Investigator's choice of chemotherapy arm, resulting in a higher Day 100 post-HSCT mortality rate.

Overall, 79/164 patients (48%) in the BESPONSA arm and 35/162 patients (22%) in the Investigator's choice of chemotherapy arm had a follow-up HSCT. The post-HSCT non-relapse mortality rate was 31/79 (39%) and 8/35 (23%) in the BESPONSA arm compared to the Investigator's choice of chemotherapy arm, respectively.

In the BESPONSA arm, the most common causes of post-HSCT non-relapse mortality included VOD and infections. Five of the 18 VOD events that occurred post-HSCT were fatal. In the BESPONSA arm, among patients with ongoing VOD at time of death, 6 patients died due to multiorgan failure (MOF) or infection (3 patients died due to MOF, 2 patients died due to infection, and 1 patient died due to MOF and infection).

In pediatric patients in Study WI203581 (ITCC-059), 26/53 patients (49%) had a follow-up HSCT. The post-HSCT non-relapse mortality rate was 7/26 (27%).

Monitor for toxicities post-HSCT, including signs and symptoms of infection and VOD [see Warnings and Precautions (5.1, 5.3)].

5.3 Myelosuppression

BESPONSA can cause myelosuppression, including thrombocytopenia and neutropenia [see Adverse Reactions (6.1)].

In adult patients in the INO-VATE ALL trial, thrombocytopenia and neutropenia occurred in 83/164 patients (51%) and 81/164 patients (49%), respectively. Grade 3 thrombocytopenia and neutropenia occurred in 23/164 patients (14%) and 33/164 patients (20%), respectively. Grade 4 thrombocytopenia and neutropenia occurred in 46/164 patients (28%) and 45/164 patients (27%), respectively. Febrile neutropenia, which may be life-threatening, occurred in 43/164 patients (26%). For patients who were in CR or CRi at the end of treatment, the recovery of platelet counts to > 50,000/mm^3 was later than 45 days after the final dose in 15/164 patients (9%) who received BESPONSA and 3/162 patients (2%) who received Investigator's choice of chemotherapy.

Complications associated with myelosuppression (including infections and bleeding/hemorrhage) occurred in patients receiving BESPONSA [see Adverse Reactions (6.1)]. Infections, including serious infections, some of which were life-threatening or fatal, occurred in 79/164 patients (48%). Fatal infections, including pneumonia, neutropenic sepsis, sepsis, septic shock, and pseudomonal sepsis, occurred in 8/164 patients (5%). Bacterial, viral, and fungal infections occurred.

Hemorrhage occurred in 54/164 patients (33%). Grade 3 or 4 hemorrhage occurred in 8/164 patients (5%), including a fatality in 1/164 patients (1%) (intra-abdominal hemorrhage). The most common type of hemorrhage was epistaxis which occurred in 24/164 patients (15%).

In pediatric patients in Study WI203581 (ITCC-059), Grade 3 or 4 thrombocytopenia occurred in 24/53 (45%) patients. Grade 3 or 4 neutropenia occurred in 21/53 (40%) patients. Infections occurred in 23/53 (43%) patients, and hemorrhage occurred in 22/53 (42%) patients. The most common types of hemorrhage were hematoma in 8/53 (15%), mouth hemorrhage in 6/53 (11%), and epistaxis in 6/53 (11%) patients [see Adverse Reactions (6.1)].

Monitor complete blood counts prior to each dose of BESPONSA and monitor for signs and symptoms of infection, bleeding/hemorrhage, or other effects of myelosuppression during treatment with BESPONSA. As appropriate, administer prophylactic anti-infectives and employ surveillance testing during and after treatment with BESPONSA. Based on the severity of myelosuppression, reduce dose, temporarily withhold, or permanently discontinue BESPONSA [see Dosage and Administration (2.3)].

5.4 Infusion Related Reactions

BESPONSA can cause infusion related reactions. In adult patients in the INO-VATE ALL trial, infusion related reactions occurred in patients who received BESPONSA. Infusion related reactions (all Grade 2) occurred in 4/164 patients (2%) [see Adverse Reactions (6.1)]. Infusion related reactions generally occurred in Cycle 1 shortly after the end of the BESPONSA infusion and resolved spontaneously or with medical management.

In pediatric patients in Study WI203581 (ITCC-059), infusion related reactions occurred in 4/53 (8%) patients [see Adverse Reactions (6.1)].

Premedicate with a corticosteroid, antipyretic, and antihistamine prior to dosing [see Dosage and Administration (2.2)].

Monitor patients closely during and for at least 1 hour after the end of infusion for the potential onset of infusion related reactions, including symptoms such as fever, chills, rash, or breathing problems. Interrupt infusion and institute appropriate medical management if an infusion related reaction occurs. Depending on the severity of the infusion related reaction, consider discontinuation of the infusion or administration of steroids and antihistamines. For severe or life-threatening infusion reactions, permanently discontinue BESPONSA [see Dosage and Administration (2.3)].

5.5 QT Interval Prolongation

BESPONSA can cause QT interval prolongation. In adult patients in the INO-VATE ALL trial, increases in QT interval corrected for heart rate using Fridericia’s formula (QTcF) of ≥ to 60 msec from baseline occurred in 4/162 patients (3%). Grade 2 QT prolongation was reported in 2/164 patients (1%) [see Adverse Reactions (6.1) and Clinical Pharmacology (12.2)].

In pediatric patients in Study WI203581 (ITCC-059), increases in QTcF of > 60 msec from baseline occurred in 7/49 (14%) patients. 3/52 (6%) of patients had QTcF values > 500 msec [see Adverse Reactions (6.1)].

Administer BESPONSA with caution in patients who have a history of or predisposition for QTc prolongation, who are taking medicinal products that are known to prolong QT interval [see Drug Interactions (7)], and in patients with electrolyte disturbances [see Drug Interactions (7)]. Obtain electrocardiograms (ECGs) and electrolytes prior to the start of treatment, after initiation of any drug known to prolong QTc, and periodically monitor as clinically indicated during treatment [see Drug Interactions (7), Clinical Pharmacology (12.2)]).

5.6 Embryo-Fetal Toxicity

Based on its mechanism of action and findings from animal studies, BESPONSA can cause embryo-fetal harm when administered to a pregnant woman. In animal studies, inotuzumab ozogamicin caused embryo-fetal toxicities, starting at a dose that was approximately 0.4 times the exposure in patients at the maximum recommended dose, based on the area under the concentration-time curve (AUC). Advise females of reproductive potential to use effective contraception during treatment with BESPONSA and for 8 months after the last dose. Advise males with female partners of reproductive potential to use effective contraception during treatment with BESPONSA and for 5 months after the last dose. Advise pregnant women of the potential risk to the fetus. Advise women to contact their healthcare provider if they become pregnant or if pregnancy is suspected during treatment with BESPONSA [see Use in Specific Populations (8.1, 8.3), Clinical Pharmacology (12.1), Nonclinical Toxicology (13.1)].

6. ADVERSE REACTIONS

The following adverse reactions are discussed in greater detail in other sections of the label:

- Hepatotoxicity, including hepatic VOD (also known as SOS) [see Warnings and Precautions (5.1)]
- Increased risk of post-transplant non-relapse mortality [see Warnings and Precautions (5.2)]
- Myelosuppression [see Warnings and Precautions (5.3)]
- Infusion related reactions [see Warnings and Precautions (5.4)]
- QT interval prolongation [see Warnings and Precautions (5.5)]

6.1 Clinical Trials Experience

Because clinical trials are conducted under widely varying conditions, adverse reaction rates observed in the clinical trials of a drug cannot be directly compared to rates in the clinical trials of another drug and may not reflect the rates observed in practice.

Relapsed or Refractory B-cell Precursor ALL

Adult Patients

The safety of BESPONSA was evaluated in adult patients with relapsed or refractory B-cell precursor ALL in the INO-VATE ALL trial. The study was a randomized clinical study of BESPONSA (n=164) versus Investigator’s choice of chemotherapy (fludarabine + cytarabine + granulocyte colony-stimulating factor [FLAG], mitoxantrone + cytarabine [MXN/Ara-C], or high dose cytarabine [HIDAC]) (n=143) [see Clinical Studies (14)].

Of the 164 patients who received BESPONSA, the median age was 47 years (range: 18–78 years), 56% were male, 68% had received 1 prior treatment regimen for ALL, 31% had received 2 prior treatment regimens for ALL, 68% were White, 19% were Asian, and 2% were Black.

In patients who received BESPONSA, the median duration of treatment was 8.9 weeks (range: 0.1–26.4 weeks), with a median of 3 treatment cycles started in each patient. In patients who received Investigator's choice of chemotherapy, the median duration of treatment was 0.9 weeks (range: 0.1–15.6 weeks), with a median of 1 treatment cycle started in each patient.

In patients who received BESPONSA, the most common (≥ 20%) adverse reactions were thrombocytopenia, neutropenia, infection, anemia, leukopenia, fatigue, hemorrhage, pyrexia, nausea, headache, febrile neutropenia, transaminases increased, abdominal pain, gamma-glutamyltransferase increased, and hyperbilirubinemia.

In patients who received BESPONSA, the most common (≥ 2%) serious adverse reactions were infection, febrile neutropenia, hemorrhage, abdominal pain, pyrexia, VOD, and fatigue.

In patients who received BESPONSA, the most common (≥ 2%) adverse reactions reported as the reason for permanent discontinuation were infection (6%), thrombocytopenia (2%), hyperbilirubinemia (2%), transaminases increased (2%), and hemorrhage (2%); the most common (≥ 5%) adverse reactions reported as the reason for dosing interruption were neutropenia (17%), infection (10%), thrombocytopenia (10%), transaminases increased (6%), and febrile neutropenia (5%); and the most common (≥ 1%) adverse reactions reported as the reason for dose reduction were neutropenia (1%), thrombocytopenia (1%), and transaminases increased (1%).

VOD was reported in 23/164 patients (14%) who received BESPONSA during or following treatment or following a HSCT after completion of treatment [see Warnings and Precautions (5.1)].

Table 7 shows the adverse reactions with ≥ 10% incidence reported in patients with relapsed or refractory ALL who received BESPONSA or Investigator's choice of chemotherapy.

Table 7. Adverse Reactions With ≥ 10% Incidence [Only adverse reactions with ≥ 10% incidence in the BESPONSA arm are included.] in Adult Patients With Relapsed or Refractory B-Cell Precursor ALL Who Received BESPONSA or Investigator's Choice of Chemotherapy (FLAG, MXN/Ara-C, or HIDAC)
Body System Adverse Reaction | BESPONSA (N=164) |  | FLAG, MXN/Ara-C, or HIDAC (N=143 [19 patients randomized to FLAG, MXN/Ara-C, or HIDAC did not receive treatment.])
Body System Adverse Reaction | All Grades | ≥ Grade 3 | All Grades | ≥ Grade 3
Body System Adverse Reaction | % | % | % | %
Infections
Infection [Infection includes any reported preferred terms for BESPONSA retrieved in the System Organ Class Infections and infestations.] | 48 | 28 | 76 | 54
Blood and lymphatic system disorders
Thrombocytopenia [Thrombocytopenia includes the following reported preferred terms: Platelet count decreased and Thrombocytopenia.] | 51 | 42 | 61 | 59
Neutropenia [Neutropenia includes the following reported preferred terms: Neutropenia and Neutrophil count decreased.] | 49 | 48 | 45 | 43
Anemia [Anemia includes the following reported preferred terms: Anemia and Hemoglobin decreased.] | 36 | 24 | 59 | 47
Leukopenia [Leukopenia includes the following reported preferred terms: Leukopenia, Monocytopenia, and White blood cell count decreased.] | 35 | 33 | 43 | 42
Febrile neutropenia | 26 | 26 | 53 | 53
Lymphopenia [Lymphopenia includes the following reported preferred terms: B-lymphocyte count decreased, Lymphocyte count decreased, and Lymphopenia.] | 18 | 16 | 27 | 26
Metabolism and nutrition disorders
Decreased appetite | 12 | 1 | 13 | 2
Nervous system disorders
Headache [Headache includes the following reported preferred terms: Headache, Migraine, and Sinus headache.] | 28 | 2 | 27 | 1
Vascular disorders
Hemorrhage [Hemorrhage includes reported preferred terms for BESPONSA retrieved in the Standard MedDRA Query (narrow) for Hemorrhage terms (excluding laboratory terms), resulting in the following preferred terms: Conjunctival hemorrhage, Contusion, Ecchymosis, Epistaxis, Eyelid bleeding, Gastrointestinal hemorrhage, Gastritis hemorrhagic, Gingival bleeding, Hematemesis, Hematochezia, Hematotympanum, Hematuria, Hemorrhage intracranial, Hemorrhage subcutaneous, Hemorrhoidal hemorrhage, Intra-abdominal hemorrhage, Lip hemorrhage, Lower gastrointestinal hemorrhage, Mesenteric hemorrhage, Metrorrhagia, Mouth hemorrhage, Muscle hemorrhage, Oral mucosa hematoma, Petechiae, Post-procedural hematoma, Rectal hemorrhage, Shock hemorrhagic, Subcutaneous hematoma, Subdural hematoma, Upper gastrointestinal hemorrhage, and Vaginal hemorrhage.] | 33 | 5 | 28 | 5
Gastrointestinal disorders
Nausea | 31 | 2 | 46 | 0
Abdominal pain [Abdominal pain includes the following reported preferred terms: Abdominal pain, Abdominal pain lower, Abdominal pain upper, Abdominal tenderness, Esophageal pain, and Hepatic pain.] | 23 | 3 | 23 | 1
Diarrhea | 17 | 1 | 38 | 1
Constipation | 16 | 0 | 24 | 0
Vomiting | 15 | 1 | 24 | 0
Stomatitis [Stomatitis includes the following reported preferred terms: Aphthous ulcer, Mucosal inflammation, Mouth ulceration, Oral pain, Oropharyngeal pain, and Stomatitis.] | 13 | 2 | 26 | 3
Hepatobiliary disorders
Hyperbilirubinemia | 21 | 5 | 17 | 6
General disorders and administration site conditions
Fatigue [Fatigue includes the following reported preferred terms: Asthenia and Fatigue.] | 35 | 5 | 25 | 3
Pyrexia | 32 | 3 | 42 | 6
Chills | 11 | 0 | 11 | 0
Investigations
Transaminases increased [Transaminases increased includes the following reported preferred terms: Aspartate aminotransferase increased, Alanine aminotransferase increased, Hepatocellular injury, and Hypertransaminasemia.] | 26 | 7 | 13 | 5
Gamma-glutamyltransferase increased | 21 | 10 | 8 | 4
Alkaline phosphatase increased | 13 | 2 | 7 | 0
Adverse reactions included treatment-emergent all-causality events that commenced on or after Cycle 1 Day 1 within 42 days after the final dose of BESPONSA, but prior to the start of a new anticancer treatment (including HSCT).
Preferred terms were retrieved by applying the Medical Dictionary for Regulatory Activities (MedDRA) version 18.1.
Severity grade of adverse reactions were according to NCI CTCAE version 3.0.
Abbreviations: ALL=acute lymphoblastic leukemia; FLAG=fludarabine + cytarabine + granulocyte colony-stimulating factor; HIDAC=high dose cytarabine; HSCT=hematopoietic stem cell transplant; MXN/Ara-C=mitoxantrone + cytarabine; N=number of patients; NCI CTCAE=National Cancer Institute Common Toxicity Criteria for Adverse Events.

Additional adverse reactions (all grades) that were reported in less than 10% of patients treated with BESPONSA included: lipase increased (9%), abdominal distension (6%), amylase increased (5%), hyperuricemia (4%), ascites (4%), infusion related reaction (2%; includes the following: hypersensitivity and infusion related reaction), pancytopenia (2%; includes the following: bone marrow failure, febrile bone marrow aplasia, and pancytopenia), tumor lysis syndrome (2%), and electrocardiogram QT prolonged (1%).

Table 8 shows the clinically important laboratory abnormalities reported in patients with relapsed or refractory ALL who received BESPONSA or Investigator's choice of chemotherapy.

Table 8. Laboratory Abnormalities in Patients With Relapsed or Refractory B-Cell Precursor ALL Who Received BESPONSA or Investigator's Choice of Chemotherapy (FLAG, MXN/Ara-C, or HIDAC)
 |  | BESPONSA |  |  | FLAG, MXN/Ara-C, or HIDAC
 |  | All Grades | Grade 3/4 |  | All Grades | Grade 3/4
Laboratory Abnormality [Laboratory abnormalities were summarized up to the end of treatment + 42 days but prior to the start of a new anti-cancer therapy.] | N | % | % | N | % | %
Hematology
Platelet count decreased | 161 | 98 | 76 | 142 | 100 | 99
Hemoglobin decreased | 161 | 94 | 40 | 142 | 100 | 70
Leukocytes decreased | 161 | 95 | 82 | 142 | 99 | 98
Neutrophil count decreased | 160 | 94 | 86 | 130 | 93 | 88
Lymphocytes (absolute) decreased | 160 | 93 | 71 | 127 | 97 | 91
Chemistry
GGT increased | 148 | 67 | 18 | 111 | 68 | 17
AST increased | 160 | 71 | 4 | 134 | 38 | 4
ALP increased | 158 | 57 | 1 | 133 | 52 | 3
ALT increased | 161 | 49 | 4 | 137 | 46 | 4
Blood bilirubin increased | 161 | 36 | 5 | 138 | 35 | 6
Lipase increased | 139 | 32 | 13 | 90 | 20 | 2
Hyperuricemia | 158 | 16 | 3 | 122 | 11 | 0
Amylase increased | 143 | 15 | 2 | 102 | 9 | 1
Severity grade of laboratory abnormalities according to NCI CTCAE version 3.0.
Abbreviations: ALL=acute lymphoblastic leukemia; ALP=alkaline phosphatase; ALT=alanine aminotransferase; AST=aspartate aminotransferase; FLAG=fludarabine + cytarabine + granulocyte colony-stimulating factor; GGT=gamma-glutamyltransferase; HIDAC=high dose cytarabine; MXN/Ara-C=mitoxantrone + cytarabine; N=number of patients; NCI CTCAE=National Cancer Institute Common Toxicity Criteria for Adverse Events.

Pediatric Patients

The safety of BESPONSA in pediatric patients 1 year and older with relapsed or refractory CD22-positive B-cell precursor ALL was evaluated in a multicenter, single-arm, open-label study (ITCC-059) [see Clinical Studies (14)]. Patients (n=53) received the recommended dosage of BESPONSA [see Dosage and Administration (2.1)] or BESPONSA at an initial dose of 1.4 mg/m^2/cycle (approximately 0.78 times the recommended initial dosage). Patients received BESPONSA for a median of 2 (range: 1-4) cycles. The median age of patients who received BESPONSA was 9 years (range: 1-17), with 68% male.

Serious adverse reactions occurred in 62% of patients who received BESPONSA. Serious adverse reactions in > 2% of patients included infection (21%), febrile neutropenia (17%), VOD (15%), hemorrhage (4%), pyrexia (6%) and multiorgan failure (2%). Fatal adverse reactions occurred in 8% of patients who received BESPONSA, including multiorgan failure, lung infection, sepsis, and encephalopathy.

Permanent discontinuation of BESPONSA due to an adverse reaction occurred in 21% of patients. Adverse reactions which resulted in permanent discontinuation of BESPONSA in 2 or more patients included ALT increased and platelet count decreased.

Dosage interruptions of BESPONSA due to an adverse reaction occurred in 11% of patients. Adverse reactions which required dosage interruption of BESPONSA in 6 patients included increased transaminases, febrile neutropenia, and headache.

The most common adverse reactions (≥ 20%), including laboratory abnormalities, were thrombocytopenia, pyrexia, anemia, vomiting, infection, hemorrhage, neutropenia, nausea, leukopenia, febrile neutropenia, increased transaminases, abdominal pain, and headache.

Table 9 summarizes the adverse reactions in ITCC-059.

Table 9. Adverse Reactions (≥ 5%) in Pediatric Patients (N=53) With CD22-Positive Relapsed or Refractory ALL in Study WI203581 (ITCC-059)
Body System; Adverse Reaction | BESPONSA Monotherapy; (N=53)
Body System; Adverse Reaction | All Grades | ≥ Grade 3
Body System; Adverse Reaction | % | %
General disorders and administration site conditions
Pyrexia | 49 | 4
Edema [Includes other related terms.] | 19 | 0
Fatigue | 17 | 0
Pain | 15 | 2
Chills | 8 | 0
Blood and lymphatic system disorders
Anemia | 45 | 38
Febrile neutropenia | 28 | 28
Gastrointestinal disorders
Vomiting | 45 | 2
Nausea | 32 | 0
Abdominal pain | 25 | 2
Constipation | 19 | 2
Stomatitis | 17 | 6
Diarrhea | 11 | 0
Infections and infestations
Infection [Infection includes any reported preferred terms for system organ class infections and infestations resulting in the following preferred terms: Acinetobacter bacteremia, bacteremia, candida infection, Cytomegalovirus infection, device related infection, device related sepsis, encephalitis, infectious enterocolitis, fungal infection, herpes virus infection, herpes zoster, influenza, kidney infection, mucosal infection, otitis media, paronychia, pneumonia, pneumonia fungal, respiratory tract infection, rhinitis, sepsis, sinusitis, skin infection, stoma site infection, upper respiratory tract infection, urinary tract inflammation, urinary tract infection, vaginal infection.] | 43 | 23
Vascular disorders
Hemorrhage [Hemorrhage includes any reported PT terms within the hemorrhage terms (excl laboratory terms) (SMQ) narrow, resulting in the following preferred terms: catheter site hemorrhage, diarrhea hemorrhagic, epistaxis, gingival bleeding, hematemesis, hematoma, hematuria, hemoptysis, hemorrhage intracranial, hemorrhoidal hemorrhage, lip hemorrhage, mouth hemorrhage, oral blood blister, petechiae, purpura, thrombotic thrombocytopenic purpura, and upper gastrointestinal hemorrhage.] | 42 | 6
Hypotension | 6 | 4
Nervous system disorders
Headache | 21 | 0
Skin and subcutaneous tissue disorders
Rash | 19 | 4
Pruritis | 9 | 0
Hyperhidrosis | 6 | 0
Musculoskeletal and connective tissue disorders
Pain in extremity | 19 | 2
Back pain | 6 | 0
Neck pain | 6 | 0
Muscular weakness | 6 | 0
Respiratory, thoracic and mediastinal disorders
Cough | 17 | 0
Dyspnea | 8 | 2
Hypoxia | 8 | 4
Hepatobiliary disorders
Veno-occlusive disease | 15 | 13
Hyperbilirubinemia | 9 | 8
Metabolism and nutrition disorders
Decreased appetite | 11 | 4
Tumor lysis syndrome | 11 | 11
Investigations
Weight increased | 8 | 2
Injury, poisoning and procedural complications
Infusion related reaction [Infusion related reaction includes the following preferred terms: infusion-related reaction and hypersensitivity.] | 8 | 0
Cardiac disorders
Sinus tachycardia | 6 | 2
Psychiatric disorders
Anxiety | 6 | 0
Severity grade of adverse reactions were according to NCI CTCAE version 4.03.

Table 10 summarizes select laboratory abnormalities in pediatric patients with CD22-positive relapsed/refractory ALL after receiving BESPONSA monotherapy in Study WI203581 (ITCC-059).

Table 10. Select Laboratory Abnormalities in Pediatric Patients with CD22-positive Relapsed/Refractory ALL after receiving BESPONSA Monotherapy in Study WI203581 (ITCC-059)
Laboratory Abnormality |  | BESPONSA Monotherapy
Laboratory Abnormality |  | All Grades | Grade 3/4
Laboratory Abnormality | N | % | %
Hematology
Platelet count decreased | 53 | 100 | 85
Neutrophil count decreased | 53 | 98 | 96
White blood cell decreased | 53 | 98 | 89
Hemoglobin decreased | 53 | 96 | 42
Lymphocyte count decreased | 52 | 87 | 73
Chemistry
AST increased | 53 | 87 | 21
ALT increased | 53 | 83 | 21
GGT increased | 33 | 79 | 27
Blood bilirubin increased | 53 | 30 | 9
ALP increased | 53 | 28 | 0
Lipase increased | 48 | 23 | 4
Serum amylase increased | 49 | 14 | 0
Severity grade of laboratory abnormalities according to NCI CTCAE version 4.03.
Abbreviations: N= number of subjects with valid post-baseline assessment; NCI CTCAE=National Cancer Institute Common Toxicity Criteria for Adverse Events.

7. DRUG INTERACTIONS

Drugs That Prolong the QT Interval

Concomitant use of BESPONSA with drugs known to prolong the QT interval or induce Torsades de Pointes may increase the risk of a clinically significant QTc interval prolongation [see Clinical Pharmacology (12.2)]. Discontinue or use alternative concomitant drugs that do not prolong QT/QTc interval while the patient is using BESPONSA. When it is not feasible to avoid concomitant use of drugs known to prolong QT/QTc, obtain ECGs and electrolytes prior to the start of treatment, after initiation of any drug known to prolong QTc, and periodically monitor as clinically indicated during treatment [see Warnings and Precautions (5.5)].

8. USE IN SPECIFIC POPULATIONS

8.1 Pregnancy

Risk Summary

Based on its mechanism of action and findings from animal studies [see Clinical Pharmacology (12.1), Nonclinical Toxicology (13.1)], BESPONSA can cause embryo-fetal harm when administered to a pregnant woman. There are no available data on BESPONSA use in pregnant women to inform a drug-associated risk. In rat embryo-fetal development studies, inotuzumab ozogamicin caused embryo-fetal toxicity at maternal systemic exposures that were ≥ 0.4 times the exposure in patients at the maximum recommended dose, based on AUC [see Data]. Advise patients of the potential risk to a fetus.

In the U.S. general population, the estimated background risk of major birth defects and miscarriage in clinically recognized pregnancies are 2–4% and 15–20%, respectively.

Data

Animal Data

In embryo-fetal development studies in rats, pregnant animals received daily intravenous doses of inotuzumab ozogamicin up to 0.36 mg/m^2 during the period of organogenesis. Embryo-fetal toxicities including increased resorptions and fetal growth retardation as evidenced by decreased live fetal weights and delayed skeletal ossification were observed at ≥ 0.11 mg/m^2 (approximately 2 times the exposure in patients at the maximum recommended dose, based on AUC). Fetal growth retardation also occurred at 0.04 mg/m^2 (approximately 0.4 times the exposure in patients at the maximum recommended dose, based on AUC).

In an embryo-fetal development study in rabbits, pregnant animals received daily intravenous doses up to 0.15 mg/m^2 (approximately 3 times the exposure in patients at the maximum recommended dose, based on AUC) during the period of organogenesis. At a dose of 0.15 mg/m^2, slight maternal toxicity was observed in the absence of any effects on embryo‑fetal development.

8.2 Lactation

Risk Summary

There are no data on the presence of inotuzumab ozogamicin or its metabolites in human milk, the effects on the breastfed child, or the effects on milk production. Because of the potential for serious adverse reactions in a breastfed child, advise women not to breastfeed during treatment with BESPONSA and for 2 months after the last dose.

8.3 Females and Males of Reproductive Potential

Based on its mechanism of action and findings from animal studies, BESPONSA can cause embryo-fetal harm when administered to a pregnant woman [see Use in Specific Populations (8.1)].

Pregnancy Testing

Verify the pregnancy status of females of reproductive potential prior to initiating BESPONSA.

Contraception

Females

Advise females of reproductive potential to use effective contraception during treatment with BESPONSA and for 8 months after the last dose [see Nonclinical Toxicology (13.1)].

Males

Advise males with female partners of reproductive potential to use effective contraception during treatment with BESPONSA and for 5 months after the last dose [see Nonclinical Toxicology (13.1)].

Infertility

Females

Based on findings in animals, BESPONSA may impair fertility in females of reproductive potential [see Nonclinical Toxicology (13.1)].

Males

Based on findings in animals, BESPONSA may impair fertility in males of reproductive potential [see Nonclinical Toxicology (13.1)].

8.4 Pediatric Use

The safety and effectiveness of BESPONSA in pediatric patients 1 year and older with relapsed or refractory CD22-positive B-cell precursor ALL have been established. The use of BESPONSA for this indication is supported by evidence of safety and effectiveness in Study WI203581 (ITCC-059) [see Adverse Reactions (6.1), Clinical Studies (14.1)]. The study included patients in the following age groups: 2 patients 1 year to < 2 years old, 10 patients 2 years to < 6 years old, 20 patients 6 years to < 12 years old, and 20 patients 12 years to < 17 years old. Compared to adults, pediatric patients had a higher incidence of liver test abnormalities; with grade 3-4 increases in AST, ALT, and total bilirubin in 21%, 21%, and 9%, respectively, in pediatric patients treated with BESPONSA compared to 4%, 4%, and 5% in adults.

The safety and effectiveness of BESPONSA in patients < 1 year of age with relapsed or refractory CD22-positive B-cell precursor ALL have not been established.

8.5 Geriatric Use

In the INO-VATE ALL trial, 30/164 patients (18%) treated with BESPONSA were ≥ 65 years of age. No differences in responses were identified between older and younger patients.

Based on a population pharmacokinetic analysis in 765 patients, no adjustment to the starting dose is required based on age [see Clinical Pharmacology (12.3)].

8.6 Hepatic Impairment

Based on a population pharmacokinetic analysis, the clearance of inotuzumab ozogamicin in patients with mild hepatic impairment (total bilirubin less than or equal to ULN and AST greater than ULN, or total bilirubin greater than 1.0–1.5 × ULN and AST any level; n=150) was similar to patients with normal hepatic function (total bilirubin/AST less than or equal to ULN; n=611). In patients with moderate (total bilirubin greater than 1.5–3 × ULN and AST any level; n=3) and severe hepatic impairment (total bilirubin greater than 3 × ULN and AST any level; n=1), inotuzumab ozogamicin clearance did not appear to be reduced [see Clinical Pharmacology (12.3)].

No adjustment to the starting dose is required when administering BESPONSA to patients with total bilirubin less than or equal to 1.5 × ULN and AST/ALT less than or equal to 2.5 × ULN [see Dosage and Administration (2.3)]. There is limited safety information available in patients with total bilirubin greater than 1.5 × ULN and/or AST/ALT greater than 2.5 × ULN prior to dosing. Interrupt dosing until recovery of total bilirubin to less than or equal to 1.5 × ULN and AST/ALT to less than or equal to 2.5 × ULN prior to each dose unless due to Gilbert's syndrome or hemolysis. Permanently discontinue treatment if total bilirubin does not recover to less than or equal to 1.5 × ULN or AST/ALT does not recover to less than or equal to 2.5 × ULN [see Dosage and Administration (2.3), Warnings and Precautions (5.1)].

11. DESCRIPTION

Inotuzumab ozogamicin is a CD22-directed antibody and cytotoxic-drug conjugate (ADC) consisting of 3 components: 1) the recombinant humanized immunoglobulin class G subtype 4 (IgG4) kappa antibody inotuzumab, specific for human CD22, 2) N-acetyl-gamma-calicheamicin that causes double-stranded DNA breaks, and 3) an acid-cleavable linker composed of the condensation product of 4-(4'-acetylphenoxy)-butanoic acid (AcBut) and 3-methyl-3-mercaptobutane hydrazide (known as dimethylhydrazide) that covalently attaches N-acetyl-gamma-calicheamicin to inotuzumab.

Inotuzumab ozogamicin has an approximate molecular weight of 160 kDa. The average number of calicheamicin derivative molecules conjugated to each inotuzumab molecule is approximately 6 with a distribution from 2–8. Inotuzumab ozogamicin is produced by chemical conjugation of the antibody and small molecule components. The antibody is produced by mammalian (Chinese hamster ovary) cells, and the semisynthetic calicheamicin derivative is produced by microbial fermentation followed by synthetic modification.

BESPONSA (inotuzumab ozogamicin) for injection is supplied as a sterile, white to off-white, preservative-free, lyophilized powder for intravenous administration. Each single-dose vial delivers 0.9 mg inotuzumab ozogamicin. Inactive ingredients are polysorbate 80 (0.36 mg), sodium chloride (2.16 mg), sucrose (180 mg), and tromethamine (8.64 mg). After reconstitution with 4 mL of Sterile Water for Injection, USP, the final concentration is 0.25 mg/mL of inotuzumab ozogamicin with a deliverable volume of 3.6 mL (0.9 mg) and a pH of approximately 8.0.

12. CLINICAL PHARMACOLOGY

12.1 Mechanism of Action

Inotuzumab ozogamicin is a CD22-directed antibody drug conjugate (ADC). Inotuzumab recognizes human CD22. The small molecule, N-acetyl-gamma-calicheamicin, is a cytotoxic agent that is covalently attached to the antibody via a linker. Nonclinical data suggest that the anticancer activity of inotuzumab ozogamicin is due to the binding of the ADC to CD22-expressing tumor cells, followed by internalization of the ADC-CD22 complex, and the intracellular release of N-acetyl-gamma-calicheamicin dimethylhydrazide via hydrolytic cleavage of the linker. Activation of N-acetyl-gamma-calicheamicin dimethylhydrazide induces double-strand DNA breaks, subsequently inducing cell cycle arrest and apoptotic cell death.

12.2 Pharmacodynamics

During the treatment period, the pharmacodynamic response to BESPONSA was characterized by the depletion of CD22-positive leukemic blasts.

Cardiac Electrophysiology

In a randomized clinical study in patients with relapsed or refractory ALL, increases in QTcF of ≥ 60 msec from baseline were measured in 4/162 patients (3%) in the BESPONSA arm and 3/124 patients (2%) in the Investigator's choice of chemotherapy arm. Increases in QTcF of > 500 msec were observed in none of the patients in the BESPONSA arm and 1/124 patients (1%) in the Investigator's choice of chemotherapy arm. Central tendency analysis of the QTcF interval changes from baseline showed that the highest mean (upper bound of the 2-sided 90% CI) for QTcF was 15.3 (21.1) msec, which was observed at Cycle 4/Day 1/1 hour in the BESPONSA arm [see Warnings and Precautions (5.5)].

12.3 Pharmacokinetics

The mean Cmax of inotuzumab ozogamicin was 308 ng/mL. The mean simulated total AUC per cycle was 100,000 ng∙h/mL. In patients with relapsed or refractory ALL, steady-state drug concentration was achieved by Cycle 4. Following administration of multiple doses, a 5.3 times accumulation of inotuzumab ozogamicin was predicted by Cycle 4.

Distribution

N-acetyl-gamma-calicheamicin dimethylhydrazide is approximately 97% bound to human plasma proteins in vitro. In humans, the total volume of distribution of inotuzumab ozogamicin was approximately 12 L.

Elimination

The pharmacokinetics of inotuzumab ozogamicin was well characterized by a 2-compartment model with linear and time-dependent clearance components. In 234 patients with relapsed or refractory ALL, the clearance of inotuzumab ozogamicin at steady state was 0.0333 L/h and the terminal half-life (t½) was 12.3 days. Following administration of multiple doses, a 5.3 times accumulation of inotuzumab ozogamicin was predicted by Cycle 4.

Metabolism

In vitro, N-acetyl-gamma-calicheamicin dimethylhydrazide was primarily metabolized via nonenzymatic reduction. In humans, N-acetyl-gamma-calicheamicin dimethylhydrazide serum levels were typically below the limit of quantitation.

Specific Populations

The effect of intrinsic factors on inotuzumab ozogamicin pharmacokinetics was assessed using a population pharmacokinetic analysis unless otherwise specified. Age (18 to 92 years of age), sex, and race (Asian versus non-Asian [Caucasian, Black, and Unspecified]) had no clinically significant effect on the pharmacokinetics of inotuzumab ozogamicin. Body surface area was found to significantly affect inotuzumab ozogamicin disposition. BESPONSA is dosed based on body surface area [see Dosage and Administration (2.1)].

Patients with Renal Impairment

The clearance of inotuzumab ozogamicin in patients with mild renal impairment (creatinine clearance [CLcr; based on the Cockcroft-Gault formula] 60–89 mL/min; n=237), moderate renal impairment (CLcr 30–59 mL/min; n=122), or severe renal impairment (CLcr 15–29 mL/min; n=4) was similar to patients with normal renal function (CLcr ≥ 90 mL/min; n=402). The safety and efficacy of inotuzumab ozogamicin in patients with end stage renal disease with or without hemodialysis is unknown.

Patients with Hepatic Impairment

The clearance of inotuzumab ozogamicin in patients with mild hepatic impairment (total bilirubin ≤ ULN and AST > ULN, or total bilirubin > 1.0–1.5 × ULN and AST any level; n=150) was similar to patients with normal hepatic function (total bilirubin/AST ≤ ULN; n=611). There is insufficient data in patients with moderate and severe hepatic impairment (total bilirubin > 1.5 ULN).

Pediatric Patients

The exposure of inotuzumab ozogamicin increases with decreasing body size at the recommended dosage. There was an approximately 30% increase in AUC of inotuzumab ozogamicin in pediatric patients 1 year and older compared with adults.

Drug Interactions

In vitro

Effect of Metabolic Pathways and Transporter Systems on BESPONSA

N-acetyl-gamma-calicheamicin dimethylhydrazide is a substrate of P-glycoprotein (P-gp).

Effect of BESPONSA on Metabolic Pathways and Transporter Systems

At clinically relevant concentrations, N-acetyl-gamma-calicheamicin dimethylhydrazide had a low potential to:

- Inhibit cytochrome P450 (CYP 450) Enzymes: CYP1A2, CYP2B6, CYP2C8, CYP2C9, CYP2C19, CYP2D6, and CYP3A4/5.
- Induce CYP450 Enzymes: CYP1A2, CYP2B6, and CYP3A4.
- Inhibit UGT Enzymes: UGT1A1, UGT1A4, UGT1A6, UGT1A9, and UGT2B7.
- Inhibit Drug Transporters: P-gp, breast cancer resistance protein (BCRP), organic anion transporter (OAT)1 and OAT3, organic cation transporter (OCT)2, and organic anion transporting polypeptide (OATP)1B1 and OATP1B3.

At clinically relevant concentrations, inotuzumab ozogamicin had a low potential to:

- Inhibit CYP450 Enzymes: CYP1A2, CYP2A6, CYP2B6, CYP2C8, CYP2C9, CYP2C19, CYP2D6, and CYP3A4/5.
- Induce CYP450 Enzymes: CYP1A2, CYP2B6, and CYP3A4.

12.6 Immunogenicity

The observed incidence of anti-drug antibodies (ADA) is highly dependent on the sensitivity and specificity of the assay. Differences in assay methods preclude meaningful comparisons of the incidence of ADA in the studies described below with the incidence of ADA in other studies, including those of inotuzumab ozogamicin.

In clinical studies of BESPONSA in patients with relapsed or refractory ALL, the immunogenicity of inotuzumab ozogamicin was evaluated using an electrochemiluminescence (ECL)‑based immunoassay to test for ADA. For patients whose sera tested positive for ADA, a cell-based assay was performed to detect neutralizing antibodies (NAb).

During a maximum 6 cycles of treatment period in clinical studies of BESPONSA in adult patients with relapsed or refractory ALL, 7/236 (3%) patients tested positive for ADA. No patients tested positive for NAb. In patients who tested positive for ADA, the presence of positive ADA did not affect clearance following inotuzumab ozogamicin treatment. Because of the low occurrence of ADA, the effect of these antibodies on safety and efficacy of inotuzumab ozogamicin is unknown.

During a maximum 4 cycles of treatment period in clinical Study WI203581 (ITCC-059) of BESPONSA in pediatric patients with relapsed or refractory ALL (n=51), no patients tested positive for ADA against inotuzumab ozogamcin.

13. NONCLINICAL TOXICOLOGY

13.1 Carcinogenesis, Mutagenesis, Impairment of Fertility

Formal carcinogenicity studies have not been conducted with inotuzumab ozogamicin. In toxicity studies, rats were dosed weekly for 4 or 26 weeks with inotuzumab ozogamicin at doses up to 4.1 mg/m^2 and 0.73 mg/m^2, respectively. After 26 weeks of dosing, rats developed hepatocellular adenomas in the liver at 0.73 mg/m^2 (approximately 2 times the exposure in patients at the maximum recommended dose, based on AUC).

Inotuzumab ozogamicin was clastogenic in vivo in the bone marrow of male mice that received single doses ≥ 1.1 mg/m^2. This is consistent with the known induction of DNA breaks by calicheamicin. N-acetyl-gamma-calicheamicin dimethylhydrazide (the cytotoxic agent released from inotuzumab ozogamicin) was mutagenic in an in vitro bacterial reverse mutation (Ames) assay.

In a female fertility and early embryonic development study, female rats were administered daily intravenous doses of inotuzumab ozogamicin up to 0.11 mg/m^2 for 2 weeks before mating through Day 7 of pregnancy. An increase in the proportion of resorptions and decrease in the number of viable embryos and gravid uterine weights were observed at the 0.11 mg/m^2 dose level (approximately 2 times the exposure in patients at the maximum recommended dose, based on AUC). Additional findings in female reproductive organs occurred in repeat-dose toxicology studies and included decreased ovarian and uterine weights, and ovarian and uterine atrophy. Findings in male reproductive organs occurred in repeat-dose toxicology studies and included decreased testicular weights, testicular degeneration, hypospermia, and prostatic and seminal vesicle atrophy. Testicular degeneration and hypospermia were nonreversible following a 4-week nondosing period. In the chronic studies of 26-weeks duration, adverse effects on reproductive organs occurred at ≥ 0.07 mg/m^2 in male rats and at 0.73 mg/m^2 in female monkeys [see Use in Specific Populations (8.3)].

14. CLINICAL STUDIES

Relapsed or Refractory ALL

INO-VATE ALL Study – Adult Patients

The safety and efficacy of BESPONSA were evaluated in INO-VATE ALL (NCT01564784) a randomized (1:1), open‑label, international, multicenter study in patients with relapsed or refractory ALL. Patients were stratified at randomization based on duration of first remission (< 12 months or ≥ 12 months, salvage treatment (Salvage 1 or 2) and patient age at randomization (< 55 or ≥ 55 years). Eligible patients were ≥ 18 years of age with Philadelphia chromosome-negative or Philadelphia chromosome-positive relapsed or refractory B-cell precursor ALL. All patients were required to have ≥ 5% bone marrow blasts and to have received 1 or 2 previous induction chemotherapy regimens for ALL. Patients with Philadelphia chromosome-positive B-cell precursor ALL were required to have disease that failed treatment with at least 1 tyrosine kinase inhibitor and standard chemotherapy. Table 1 shows the dosing regimen used to treat patients.

Among all 326 patients who were randomized to receive BESPONSA (N=164) or Investigator's choice of chemotherapy (N=162), 215 patients (66%) had received 1 prior treatment regimen for ALL and 108 patients (33%) had received 2 prior treatment regimens for ALL. The median age was 47 years (range: 18–79 years), 276 patients (85%) had Philadelphia chromosome-negative ALL, 206 patients (63%) had a duration of first remission < 12 months, and 55 patients (17%) had undergone a HSCT prior to receiving BESPONSA or Investigator's choice of chemotherapy. The two treatment groups were generally balanced with respect to the baseline demographics and disease characteristics.

All evaluable patients had B-cell precursor ALL that expressed CD22, with ≥ 90% of evaluable patients exhibiting ≥ 70% leukemic blast CD22 positivity prior to treatment, as assessed by flow cytometry performed at a central laboratory.

The efficacy of BESPONSA was established on the basis of CR, the duration of CR, and proportion of MRD-negative CR (< 1 × 10^-4 of bone marrow nucleated cells by flow cytometry) in the first 218 patients randomized. CR, duration of remission (DoR), and MRD results in the initial 218 randomized patients were consistent with those seen in all 326 randomized patients.

Among the initial 218 randomized patients, 64/88 (73%) and 21/88 (24%) of responding patients per EAC achieved CR/CRi in Cycles 1 and 2, respectively, in the BESPONSA arm, and 29/32 (91%) and 1/32 (3%) of responding patients per EAC achieved a CR/CRi in Cycles 1 and 2, respectively, in the Investigator's choice of chemotherapy arm.

Table 11 shows the efficacy results from this study.

Table 11. Efficacy Results in Patients With Relapsed or Refractory B-Cell Precursor ALL Who Received BESPONSA or Investigator's Choice of Chemotherapy (FLAG, MXN/Ara-C, or HIDAC)
 | CR [CR, per EAC, was defined as < 5% blasts in the bone marrow and the absence of peripheral blood leukemic blasts, full recovery of peripheral blood counts (platelets ≥ 100 × 10^9/L and absolute neutrophil counts [ANC] ≥ 1 × 10^9/L) and resolution of any extramedullary disease.] |  | CRi [CRi, per EAC, was defined as < 5% blasts in the bone marrow and the absence of peripheral blood leukemic blasts, incomplete recovery of peripheral blood counts (platelets < 100 × 10^9/L and/or ANC < 1 × 10^9/L) and resolution of any extramedullary disease.] |  | CR/CRi,
 | BESPONSA (N=109) | HIDAC, FLAG, or MXN/Ara-C (N=109) | BESPONSA (N=109) | HIDAC, FLAG or MXN/Ara-C (N=109) | BESPONSA (N=109) | HIDAC, FLAG, or MXN/Ara-C (N=109)
Responding (CR/CRi) patients
n (%) [95% CI] | 39 (35.8) [26.8–45.5] | 19 (17.4) [10.8–25.9] | 49 (45.0) [35.4–54.8] | 13 (11.9) [6.5–19.5] | 88 (80.7) [72.1–87.7] | 32 (29.4) [21.0–38.8]
p-value [1-sided p-value using Chi-squared test.] |  |  |  |  | < 0.0001
DoR [DoR, based on a later cutoff date than the CR/CRi, was defined for patients who achieved CR/CRi per Investigator's assessment as time since first response of CR* or CRi† per Investigator's assessment to the date of a PFS event or censoring date if no PFS event was documented.]
n | 39 | 18 | 45 | 14 | 84 | 32
Median, months [95% CI] | 8.0 [4.9–10.4] | 4.9 [2.9–7.2] | 4.6 [3.7–5.7] | 2.9 [0.6–5.7] | 5.4 [4.2–8.0] | 3.5 [2.9–6.6]
MRD-negativity [MRD-negativity was defined by flow cytometry as leukemic cells comprising < 1 × 10^-4 (< 0.01%) of bone marrow nucleated cells.]
n | 35 | 6 | 34 | 3 | 69 | 9
Rate [Rate was defined as the number of patients who achieved MRD negativity divided by the total number of patients who achieved CR/CRi per EAC.] (%) [95% CI] | 35/39 (89.7) [75.8–97.1] | 6/19 (31.6) [12.6–56.6] | 34/49 (69.4) [54.6–81.7] | 3/13 (23.1) [5.0–53.8] | 69/88 (78.4) [68.4–86.5] | 9/32 (28.1) [13.7–46.7]
Abbreviations: CI=confidence interval; CR=complete remission; CRi=complete remission with incomplete hematologic recovery; DoR=duration of remission; EAC=Endpoint Adjudication Committee; FLAG=fludarabine + cytarabine + granulocyte colony-stimulating factor; HIDAC=high-dose cytarabine; HR=hazard ratio; MRD=minimal residual disease; MXN/AraC=mitoxantrone + cytarabine; N/n=number of patients; OS=overall survival; PFS=progression-free survival.

Among the initial 218 patients, as per EAC assessment, 32/109 patients (29%) in the BESPONSA arm achieved complete remission with partial hematologic recovery (CRh; defined as < 5% blasts in the bone marrow, ANC > 0.5 × 10^9/L, and platelet counts > 50 × 10^9/L but not meeting full recovery of peripheral blood counts) versus 6/109 patients (6%) in the Investigator's choice of chemotherapy arm, and 71/109 patients (65%) in the BESPONSA arm achieved CR/CRh versus 25/109 patients (23%) in the Investigator's choice of chemotherapy arm.

Overall, 79/164 patients (48%) in the BESPONSA arm and 35/162 patients (22%) in the Investigator's choice of chemotherapy arm had a follow-up HSCT.

Figure 1 shows the analysis of overall survival (OS). The analysis of OS did not meet the pre-specified boundary for statistical significance.

Figure 1. Kaplan-Meier Curve for Overall Survival (Intent-to-Treat Population)

WI203581 (ITCC-059) – Pediatric Patients

BESPONSA was evaluated in a multicenter, single-arm, open-label study in 53 pediatric patients ≥ 1 and < 18 years of age with relapsed or refractory CD22-positive B-cell precursor ALL.

In 53 patients, there were two dose levels: an initial dose of 1.4 mg/m^2/cycle (approximately 0.78 times the recommended initial dosage) in 12 patients and 1.8 mg/m^2/cycle in 41 patients (premedications included methylprednisolone 1 mg/kg with a maximum of 50 mg, an antipyretic, and an antihistamine). Table 1 shows the dosing regimen used to treat patients. Patients received a median of 2 cycles of therapy (range: 1 to 4 cycles). The median age was 9 years (range: 1 to 17 years), and 55% of patients had second or greater relapsed B-cell precursor ALL.

Efficacy was established on the basis of the Complete Remission (CR) Rate [CR was defined as < 5% blasts in the bone marrow and the absence of peripheral blood leukemic blasts, full recovery of peripheral blood counts (platelets ≥ 100 × 10^9/L and ANC ≥ 1 × 10^9/L) and resolution of any extramedullary disease], duration of CR, and proportion of patients with MRD negative CR [MRD was defined by leukemic cells comprising < 1 × 10^-4 (< 0.01%) of bone marrow nucleated cells by flow cytometry or by PCR]. In all patients, 22/53 (42%, 95% CI 28.1-55.9%) patients achieved CR, and the median duration of CR (DOCR) was 8.2 months (95% CI: 2.6-NE). The minimal residual disease (MRD) negativity rate in patients with CR was 21/22 [95.5% (95% CI: 77.2-99.9)] based on flow cytometry, and 19/22 [86.4% (95% CI: 65.1-97.1)] based on RQ-PCR.

15. REFERENCES

1. OSHA Hazardous Drugs. OSHA. https://www.osha.gov/hazardous-drugs

16. HOW SUPPLIED/STORAGE AND HANDLING

How Supplied

BESPONSA (inotuzumab ozogamicin) for injection is supplied as a white to off-white lyophilized powder in a single-dose vial for reconstitution and further dilution. Each vial delivers 0.9 mg inotuzumab ozogamicin. Each carton (NDC 0008-0100-01) contains one single-dose vial.

Storage and Handling

Refrigerate (2-8°C; 36-46°F) BESPONSA vials and store in the original carton to protect from light. Do not freeze.

BESPONSA is a hazardous drug. Follow applicable special handling and disposal procedures.^1

17. PATIENT COUNSELING INFORMATION

Hepatotoxicity, Including Hepatic Veno-occlusive Disease (VOD) (also known as Sinusoidal Obstruction Syndrome)

Inform patients that liver problems, including severe, life-threatening, or fatal VOD, and increases in liver tests may develop during BESPONSA treatment. Inform patients that they should seek immediate medical advice if they experience symptoms of VOD, which may include elevated bilirubin, rapid weight gain, and abdominal swelling that may be painful. Inform patients that they should carefully consider the benefit/risk of BESPONSA treatment if they have a prior history of VOD or serious ongoing liver disease [see Warnings and Precautions (5.1)].

Increased Risk of Post-HSCT Non-Relapse Mortality

Inform patients that there is an increased risk of post-HSCT non-relapse mortality after receiving BESPONSA, that the most common causes of post-HSCT non-relapse mortality included infection and VOD. Advise patients to report signs and symptoms of infection [see Warnings and Precautions (5.2)].

Myelosuppression

Inform patients that decreased blood counts, which may be life-threatening, may develop during BESPONSA treatment and that complications associated with decreased blood counts may include infections, which may be life-threatening or fatal, and bleeding/hemorrhage events. Inform patients that signs and symptoms of infection, bleeding/hemorrhage, or other effects of decreased blood counts should be reported during treatment with BESPONSA [see Warnings and Precautions (5.3)].

Infusion Related Reactions

Advise patients to contact their health care provider if they experience symptoms such as fever, chills, rash, or breathing problems during the infusion of BESPONSA [see Warnings and Precautions (5.4)].

QT Interval Prolongation

Inform patients of symptoms that may be indicative of significant QTc prolongation including dizziness, lightheadedness, and syncope. Advise patients to report these symptoms and the use of all medications to their healthcare provider [see Warnings and Precautions (5.5)].

Embryo-Fetal Toxicity

Advise males and females of reproductive potential to use effective contraception during BESPONSA treatment and for 5 and 8 months after the last dose, respectively [see Use in Specific Populations (8.3)]. Advise women to contact their healthcare provider if they become pregnant, or if pregnancy is suspected, during treatment with BESPONSA. Inform the patient of the potential risk to the fetus [see Warnings and Precautions (5.6), Use in Specific Populations (8.1)].

Lactation

Advise women against breastfeeding while receiving BESPONSA and for 2 months after the last dose [see Use in Specific Populations (8.2)].

This product's label may have been updated. For current full prescribing information, please visit www.BESPONSA.com.

US License No. 003

LAB-0763-3.0

PRINCIPAL DISPLAY PANEL - 0.9 mg Vial Label

Pfizer

NDC 0008-0100-01
Rx only

BESPONSA™
(inotuzumab ozogamicin)
for Injection

0.9 mg/vial

For Intravenous Infusion Only

No Preservatives

Single-dose vial.
Discard unused portion.

PRINCIPAL DISPLAY PANEL - 0.9 mg Vial Carton

Pfizer

NDC 0008-0100-01

BESPONSA™
(inotuzumab ozogamicin)
for Injection

0.9 mg/vial

For Intravenous Infusion Only

Reconstitution and dilution
required.

No Preservatives

One Single-Dose Vial.
Discard unused portion.

Rx only